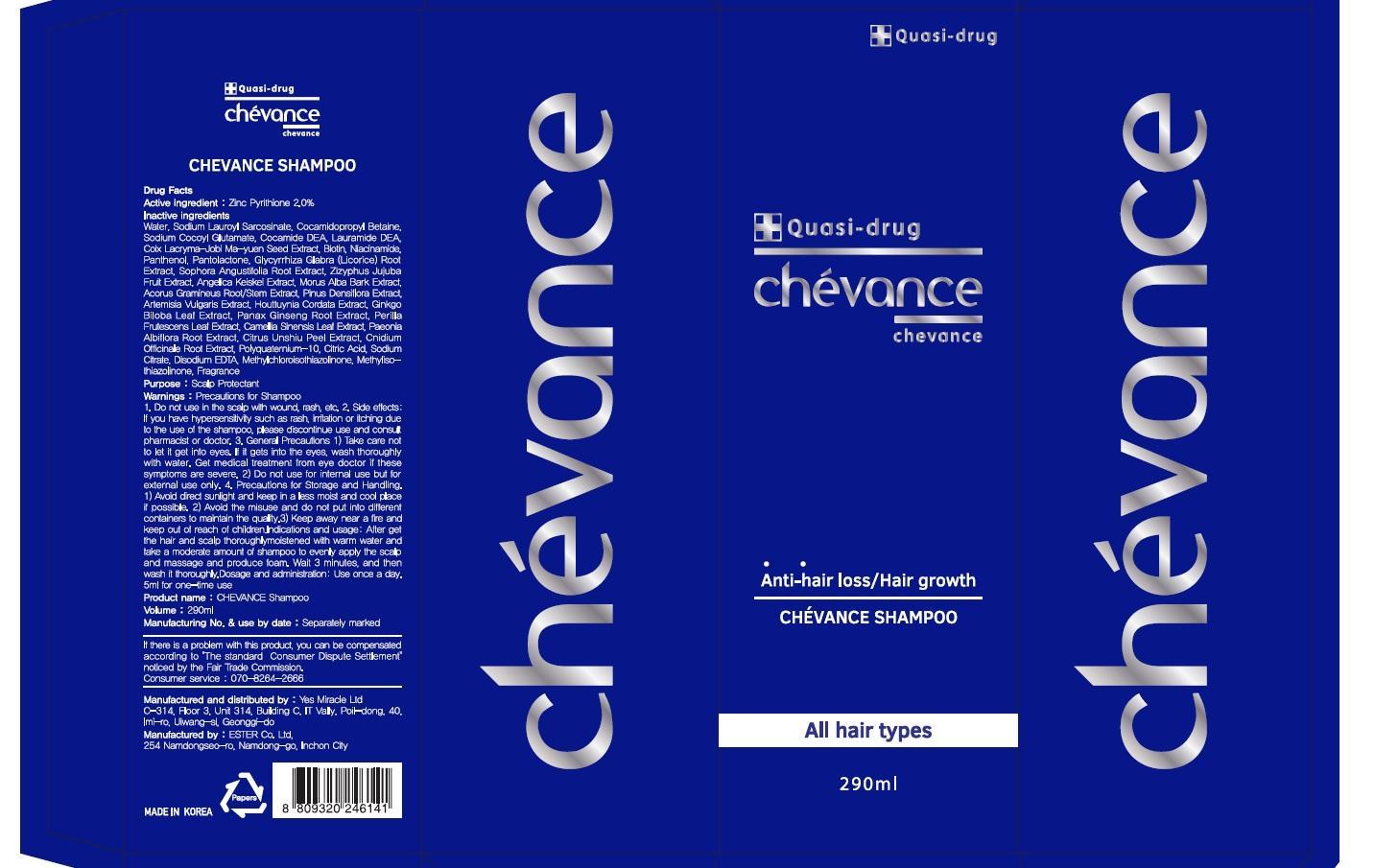 DRUG LABEL: Chevance
NDC: 70053-010 | Form: SHAMPOO
Manufacturer: Yes Miracle Ltd
Category: otc | Type: HUMAN OTC DRUG LABEL
Date: 20150821

ACTIVE INGREDIENTS: Pyrithione Zinc 5.8 mg/290 mL
INACTIVE INGREDIENTS: Water; Cocamidopropyl Betaine

ACTIVE INGREDIENT

Active Ingredient: Zinc Pyrithione 2.0%

INACTIVE INGREDIENT

Inactive Ingredients: Water, Sodium Lauroyl Sarcosinate, Cocamidopropyl Betaine, Sodium Cocoyl Glutamate, Cocamide DEA, Lauramide DEA, Coix Lacryma-Jobi Ma-yuen Seed Extract, Biotin, Niacinamide, Panthenol, Pantolactone, Glycyrrhiza Glabra (Licorice) Root Extract, Sophora Angustifolia Root Extract, Zizyphus Jujuba Fruit Extract, Angelica Keiskei Extract, Morus Alba Bark Extract, Acorus Gramineus Root/Stem Extract, Pinus Densiflora Extract, Artemisia Vulgaris Extract, Houttuynia Cordata Extract, Ginkgo Biloba Leaf Extract, Panax Ginseng Root Extract, Perilla Frutescens Leaf Extract, Camellia Sinensis Leaf Extract, Paeonia Albiflora Root Extract, Citrus Unshiu Peel Extract, Cnidium Officinale Root Extract, Polyquaternium-10, Citric Acid, Sodium Citrate, Disodium EDTA, Methylchloroisothiazolinone, Methylisothiazolinone, Fragrance

PURPOSE

Purpose: Scalp Protectant

WARNINGS

Warnings: Precautions for Shampoo 1.Do not use in the scalp with wound, sash, etc. 2.Side effects : If you have hypersensitivity sush as rash, irritation or itching due to the use of the shampoo, please discontinue use and consult pharmacist or doctor. 3.General Precautions 1)Take care not to let it get into eyes. If it gets into the eyes, wash thoroughly with water. Get medical treatment from eye doctor if these symptoms are severe. 2)Do not use for internal use but for external use only. 4.Precautions for Storage and Handling 1)Avoid direct sunlight and keep in a less moist and cool place if possible. 2)Avoid the misuse and do not put into different containers to maintain the quality. 3)Keep away near a fire and keep out of reach of children.

KEEP OUT OF REACH OF CHILDREN

INDICATIONS & USAGE

Indications & Usage: After get the hair and scalp thoroughly moistened with warm water and take a moderate amount of shampoo to evenly apply the scalp and massage and produce foam. Wait 3 minutes, and then wash it thoroughly.

DOSAGE & ADMINISTRATION

Dosage & Administration: Use once a day. 5ml for one-time use